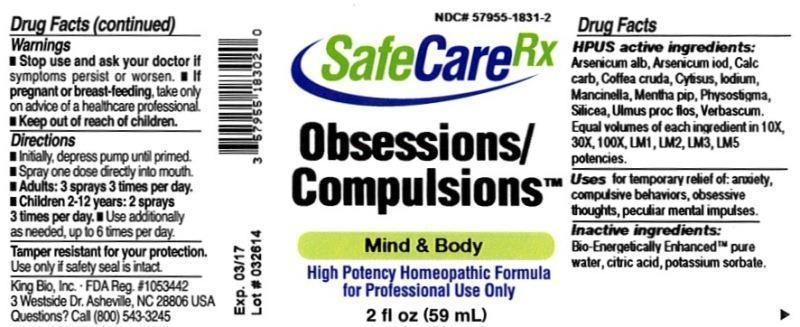 DRUG LABEL: Obsessions/Compulsions
NDC: 57955-1831 | Form: LIQUID
Manufacturer: King Bio Inc.
Category: homeopathic | Type: HUMAN OTC DRUG LABEL
Date: 20140417

ACTIVE INGREDIENTS: ARSENIC TRIOXIDE 10 [hp_X]/59 mL; ARSENIC TRIIODIDE 10 [hp_X]/59 mL; OYSTER SHELL CALCIUM CARBONATE, CRUDE 10 [hp_X]/59 mL; ARABICA COFFEE BEAN 10 [hp_X]/59 mL; CYTISUS SCOPARIUS FLOWERING TOP 10 [hp_X]/59 mL; IODINE 10 [hp_X]/59 mL; HIPPOMANE MANCINELLA FRUITING LEAFY TWIG 10 [hp_X]/59 mL; MENTHA PIPERITA 10 [hp_X]/59 mL; PHYSOSTIGMA VENENOSUM SEED 10 [hp_X]/59 mL; SILICON DIOXIDE 10 [hp_X]/59 mL; ULMUS PROCERA FLOWERING TWIG 10 [hp_X]/59 mL; VERBASCUM THAPSUS 10 [hp_X]/59 mL
INACTIVE INGREDIENTS: WATER; CITRIC ACID MONOHYDRATE; POTASSIUM SORBATE

Obsessions/Compulsions™

ACTIVE INGREDIENT

Drug Facts__________________________________________________________________________________________________________

HPUS activeingredients: Arsenicum album, Arsenicum iodatum, Calcarea carbonica, Coffea cruda, cytisus scoparius, Iodium, Mancinella, Mentha piperita, Physostigma venenosum, silicea, Ulmus procera, flos, Verbascum thapsus. Equal volumes of each ingredient in 10X, 30X, 100X,1M LM1, LM2, LM3 potencies.

INDICATIONS AND USAGE

Uses for temporary relief of: anxiety, compulsive behaviors, obsessive thoughts, peculiar mental impulses.

Inactive Ingredients:

Bio-Energetically Enhanced™ pure water, citric acid and potassium sorbate.

Warnings

- Stop use and ask your doctor if symptoms persist or worsen.
- If pregnant or breast-feeding, take only on advice of a healthcare professional.

- Keep out of reach of children

Directions

- Initially, depress pump until primed.
- Spray one dose directly into mouth.
- Adults: 3 sprays 3 times per day.
- Children 2-12 years: 2 sprays 3 times per day
- Use additionally as needed, up to 6 times per day.

OTHER SAFETY INFORMATION

Tamper resistant for your protection. Use only if safety seal is intact.

PURPOSE

Uses for temporary relief of:

- anxiety
- compulsive behaviors
- obsessive thoughts
- peculiar mental impulses.